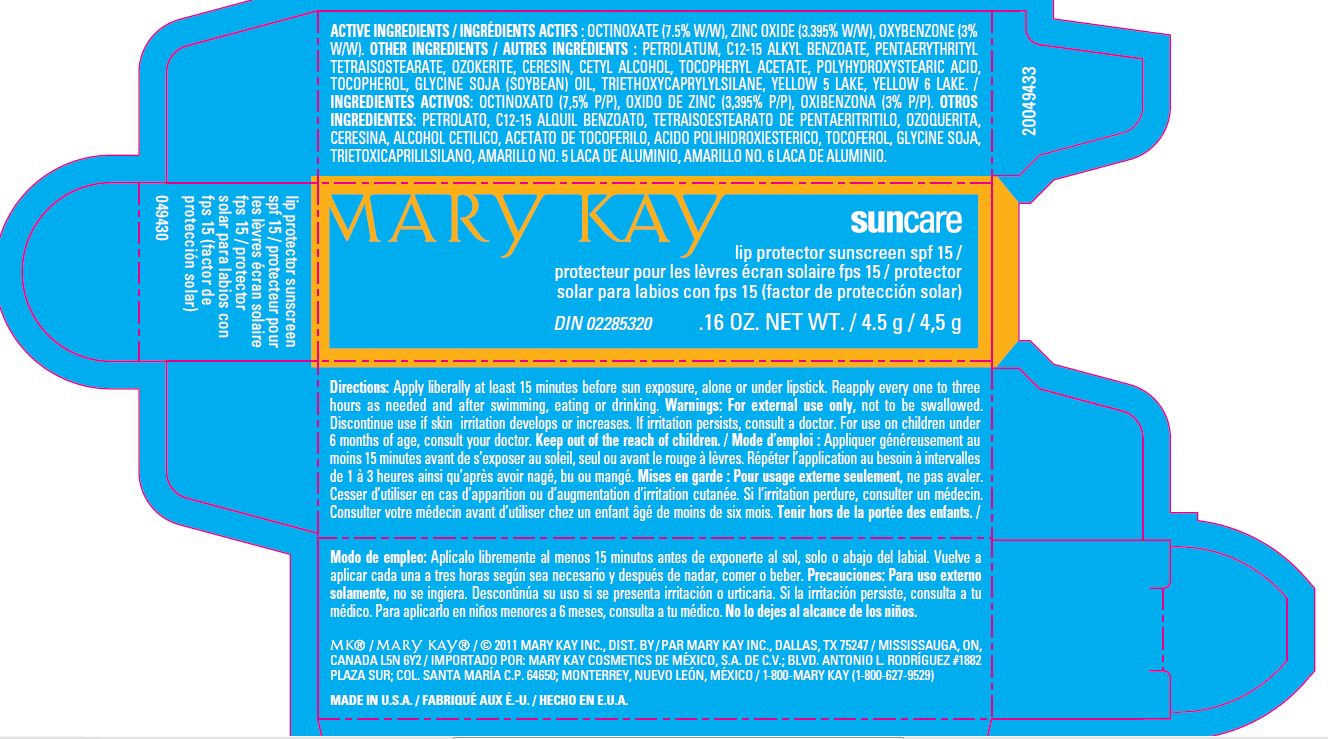 DRUG LABEL: Lip Protector Sunscreen SPF15 
NDC: 51531-9480 | Form: LIPSTICK
Manufacturer: Mary Kay INC.
Category: otc | Type: HUMAN OTC DRUG LABEL
Date: 20120301

ACTIVE INGREDIENTS: Octinoxate 0.338 g/4.5 g; Oxybenzone 0.135 g/4.5 g; Zinc Oxide 0.152 g/4.5 g
INACTIVE INGREDIENTS: PETROLATUM; ALKYL (C12-15) BENZOATE; CERESIN; CETYL ALCOHOL ; ACETATE ION; POLYHYDROXYSTEARIC ACID (2300 MW); ALPHA-TOCOPHEROL; SOYBEAN  OIL; TRIETHOXYCAPRYLYLSILANE; FD&C YELLOW NO. 5; FD&C YELLOW NO. 6

ACTIVE INGREDIENT

ACTIVE INGREDIENTS: OCTINOXATE(7.5% W/W), ZINC OXIDE(3.395% W/W),OXYBENZONE(3%W/W)

INDICATIONS AND USAGE

DIRECTION: Apply liberally at least 15 minutes before sun exposure, alone or under lipstick. Reapply every one to three hours as needed and after swimming, eating or drinking .3

WARNINGS

WARNING : For external use only. Discontinue use if irritation or rash develops. For use under 6 month of age , consult your doctor. Keep out reach of children.

INACTIVE INGREDIENT

PETROLATUM , C12-15 ALKYL BENZOATE , PENTAETYTHRITYL TETRAISOSTEARATE , OZOKERITE , CERESIN , CETYL ALCOHOL , TOCOPHERYL ACETATE, POLYHYDROXYSTERAIC ACID,TOCOPEROL , GLYCINE SOJA (SOYBEAN) OIL , TRIETHOXYCAPRYLRLSILANE , YELLOW 5 LAKE , YELLOW 6 LAKE